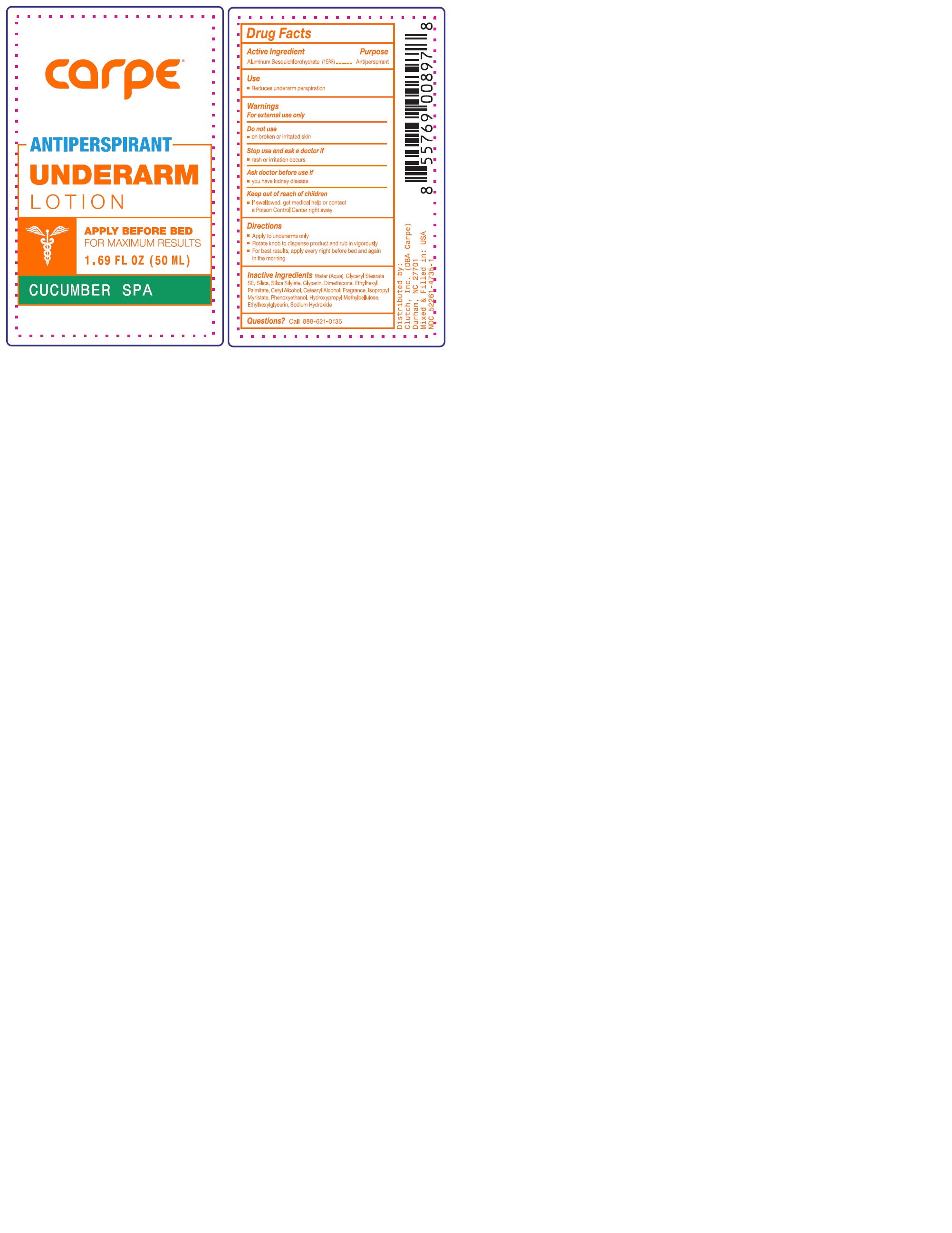 DRUG LABEL: Carpe Antiperspirant Underarm Cucumber Spa Scent
NDC: 52261-4735 | Form: Lotion
Manufacturer: Cosco International, Inc.
Category: otc | Type: HUMAN OTC DRUG LABEL
Date: 20250331

ACTIVE INGREDIENTS: Aluminum Sesquichlorohydrate 0.15 kg/1 kg
INACTIVE INGREDIENTS: water; CETOSTEARYL ALCOHOL; SILICON DIOXIDE; HEXAMETHYLDISILAZANE; GLYCERIN; ETHYLHEXYL PALMITATE; dimethicone 350; GLYCERYL STEARATE SE; phenoxyethanol; ISOPROPYL MYRISTATE; SODIUM HYDROXIDE; HYPROMELLOSE 2208 (100000 MPA.S); ethylhexylglycerin; CETYL ALCOHOL

Drug Facts

Active Ingredient Purpose
Aluminum Sesquicholorhydrate 15% .......................Anti-perspirant

PURPOSE

Anti-perspirant

Use

- Reduces underarm perspiration

Warnings

For external use only

Do not use

- on broken or irritated skin

Stop use and ask a doctor if

- rash or irritation occurs

Ask doctor before use if

- you have kidney disease

Keep out of reach of children

- If swallowed, get medical help or contact a Poison Control Center right away

Directions

- Apply to underarms only
- Rotate knob to dispense product and rub in vigorously
- For best results, apply every night before bed and again in the morning

Inactive ingredients

Water (Aqua), Glyceryl Stearate SE, Silica, Silica Silylate, Glycerin, Dimethicone, Ethylhexyl Palmitate, Cetyl Alcohol, Cetearyl Alcohol, Fragrance, Isopropyl Myristate, Phenoxyethanol, Hydroxypropyl Methylcellulose, Ethylhexylglycerin, Sodium Hydroxide

Questions?

Call 888-621-0135